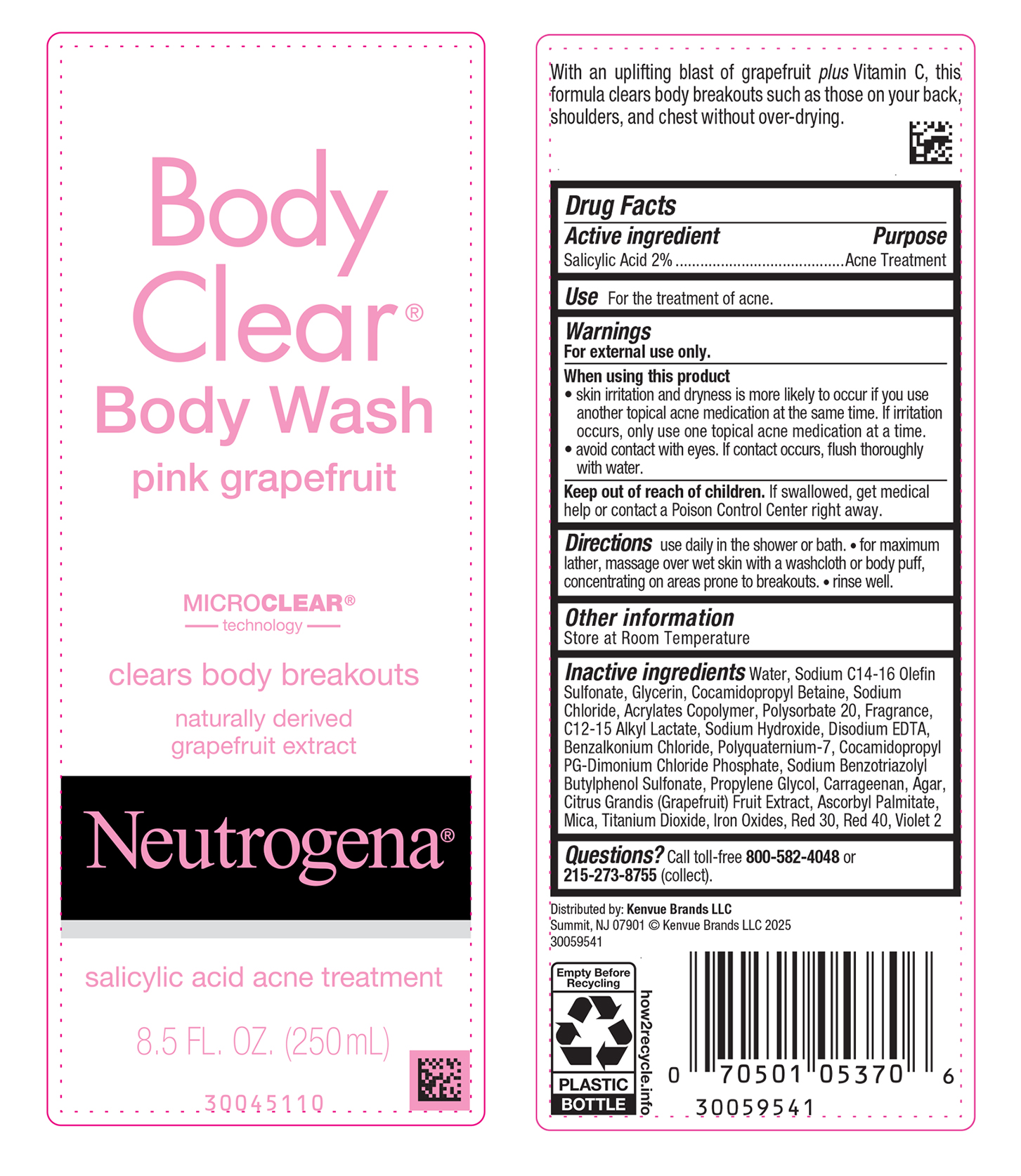 DRUG LABEL: Neutrogena Body Clear Body Wash Pink Grapefruit
NDC: 69968-0633 | Form: SUSPENSION
Manufacturer: Kenvue Brands LLC
Category: otc | Type: HUMAN OTC DRUG LABEL
Date: 20250305

ACTIVE INGREDIENTS: SALICYLIC ACID 20 mg/1 mL
INACTIVE INGREDIENTS: WATER; SODIUM C14-16 OLEFIN SULFONATE; GLYCERIN; COCAMIDOPROPYL BETAINE; SODIUM CHLORIDE; BUTYL ACRYLATE/METHYL METHACRYLATE/METHACRYLIC ACID COPOLYMER (18000 MW); POLYSORBATE 20; C12-15 ALKYL LACTATE; SODIUM HYDROXIDE; EDETATE DISODIUM ANHYDROUS; BENZALKONIUM CHLORIDE; POLYQUATERNIUM-7 (70/30 ACRYLAMIDE/DADMAC; 1600000 MW); COCAMIDOPROPYL PROPYLENE GLYCOL-DIMONIUM CHLORIDE PHOSPHATE; SODIUM BENZOTRIAZOLYL BUTYLPHENOL SULFONATE; PROPYLENE GLYCOL; CARRAGEENAN; AGAR, UNSPECIFIED; PUMMELO; ASCORBYL PALMITATE; MICA; TITANIUM DIOXIDE; FERRIC OXIDE RED; D&C RED NO. 30; FD&C RED NO. 40; D&C VIOLET NO. 2

Neutrogena® Body Clear® Body Wash pink grapefruit

Drug Facts

Active ingredient

Salicylic Acid 2%

Purpose

Acne Treatment

Use

For the treatment of acne.

Warnings

For external use only.

When using this product

- skin irritation and dryness is more likely to occur if you use another topical acne medication at the same time. If irritation occurs, only use one topical acne medication at a time.
- avoid contact with eyes. If contact occurs, flush thoroughly with water.

Keep out of reach of children. If swallowed, get medical help or contact a Poison Control Center right away.

Directions

use daily in the shower or bath.

- for maximum lather, massage over wet skin with a washcloth or body puff, concentrating on areas prone to breakouts.
- rinse well.

Other information

Store at Room Temperature

Inactive ingredients

Water, Sodium C14-16 Olefin Sulfonate, Glycerin, Cocamidopropyl Betaine, Sodium Chloride, Acrylates Copolymer, Polysorbate 20, Fragrance, C12-15 Alkyl Lactate, Sodium Hydroxide, Disodium EDTA, Benzalkonium Chloride, Polyquaternium-7, Cocamidopropyl PG-Dimonium Chloride Phosphate, Sodium Benzotriazolyl Butylphenol Sulfonate, Propylene Glycol, Carrageenan, Agar, Citrus Grandis (Grapefruit) Fruit Extract, Ascorbyl Palmitate, Mica, Titanium Dioxide, Iron Oxides, Red 30, Red 40, Violet 2

Questions?

Call toll-free 800-582-4048 or 215-273-8755 (collect).

Distributed by:

Kenvue Brands LLC
Summit, NJ 07901

PRINCIPAL DISPLAY PANEL - 250 mL Bottle Label

Body
Clear ®
Body Wash
pink grapefruit

MICRO CLEAR®
technology

clears body breakouts

naturally derived
grapefruit extract
Neutrogena®
salicylic acid acne treatment
8.5 FL. OZ. (250mL)